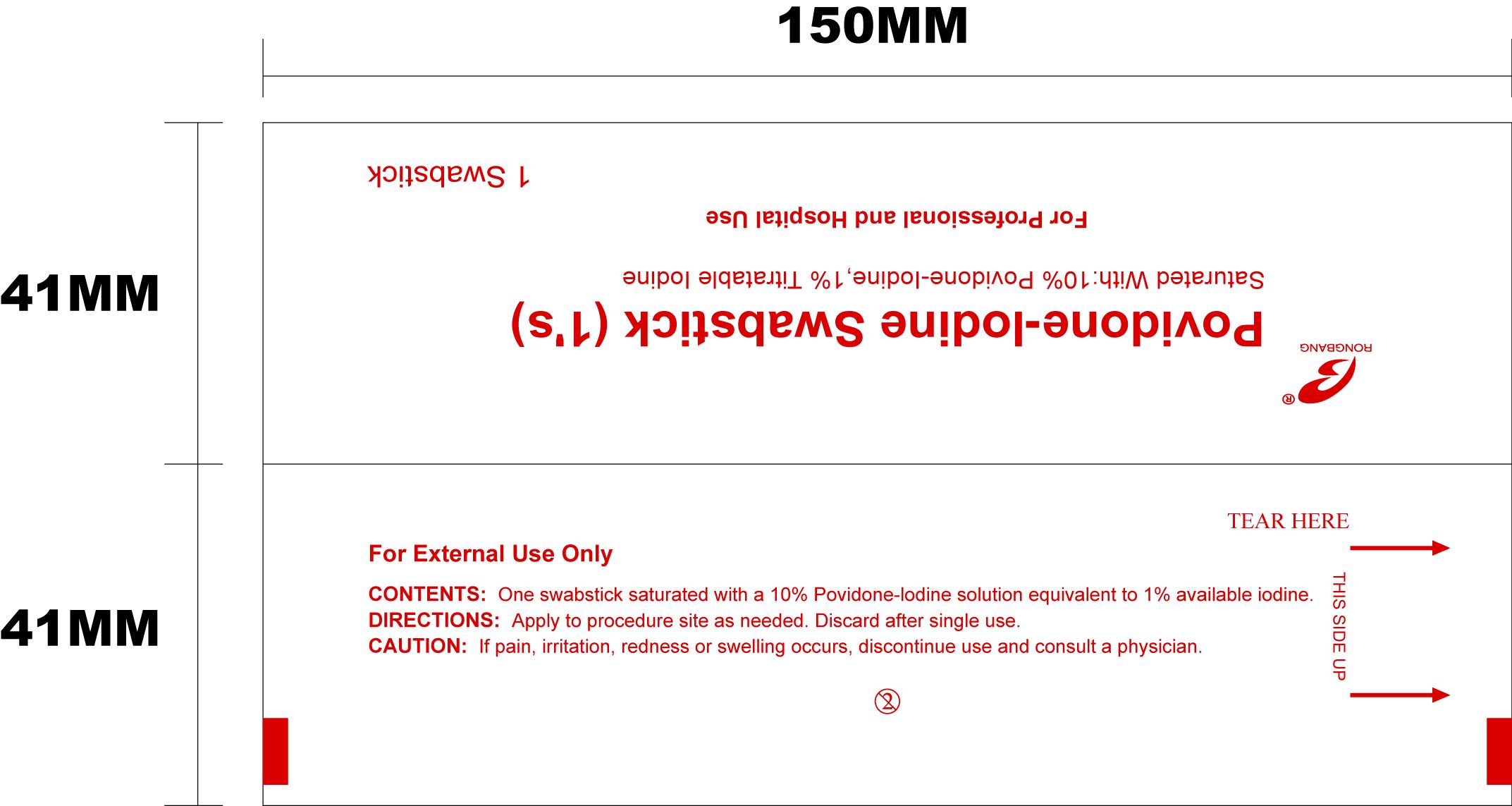 DRUG LABEL: Povidone Iodine
NDC: 49953-1893 | Form: SWAB
Manufacturer: Dalian Rongbang Medical Healthy Devices Co
Category: otc | Type: HUMAN OTC DRUG LABEL
Date: 20100702

ACTIVE INGREDIENTS: POVIDONE-IODINE 10 mL/100 mL
INACTIVE INGREDIENTS: water

Povidone Iodine Swabstick

ACTIVE INGREDIENT

Saturated with: 10% povidone-Iodine, 1% Titratable Iodine

INACTIVE INGREDIENT

Water

DOSAGE AND ADMINISTRATION

1 Swabstick. Apply to procedure site as needed.

INDICATIONS AND USAGE

For professional and hospital use

Apply to procedure site as needed. discard after single use.

WARNINGS

For professional and hospital use.

For external use only.

Discard after single use.

If pain, irritation, redness or swelling occurs, discontinue use and consult a physician.

KEEP OUT OF REACH OF CHILDREN

Professional and Hosptial use.

PURPOSE

Apply to procedure site as needed.

PACKAGE LABEL

Povidone-Iodine Swabstick (1's)

Saturated with: 10% povidone-Iodine, 1% titratable iodine.